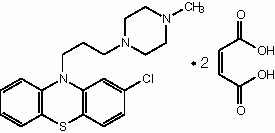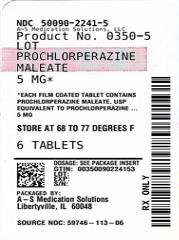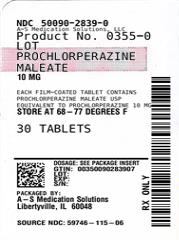 DRUG LABEL: PROCHLORPERAZINE MALEATE 
NDC: 50090-2241 | Form: TABLET
Manufacturer: A-S Medication Solutions
Category: prescription | Type: Human Prescription Drug Label
Date: 20260220

ACTIVE INGREDIENTS: PROCHLORPERAZINE MALEATE 5 mg/1 1
INACTIVE INGREDIENTS: HYDROXYPROPYL METHYLCELLULOSE; Lactose Monohydrate; Magnesium Stearate; CELLULOSE, MICROCRYSTALLINE; Polyethylene Glycol, Unspecified; PEG-20 SORBITAN OLEATE; Starch, Corn; Stearic Acid; Titanium Dioxide; KI203; ALUMINA; Fd&c Blue No. 2; KI5

PROCHLORPERAZINE MALEATE TABLETS, USP
Rx Only

WARNING

Increased Mortality in Elderly Patients with Dementia-Related Psychosis
Elderly patients with dementia-related psychosis treated with antipsychotic drugs are at an increased risk of death. Analyses of seventeen placebo-controlled trials (modal duration of 10 weeks), largely in patients taking atypical antipsychotic drugs, revealed a risk of death in drug-treated patients of between 1.6 to 1.7 times the risk of death in placebo-treated patients. Over the course of a typical 10-week controlled trial, the rate of death in drug-treated patients was about 4.5% compared to a rate of about 2.6% in the placebo group. Although the causes of death were varied, most of the deaths appeared to be either cardiovascular (e.g., heart failure, sudden death) or infectious (e.g., pneumonia) in nature. Observational studies suggest that, similar to atypical antipsychotic drugs, treatment with conventional antipsychotic drugs may increase mortality. The extent to which the findings of increased mortality in observational studies may be attributed to the antipsychotic drug as opposed to some characteristic(s) of the patients is not clear. Prochlorperazine maleate is not approved for the treatment of patients with dementia-related psychosis (see WARNINGS).

DESCRIPTION

Prochlorperazine, USP is a phenothiazine derivative, present in prochlorperazine tablets as the maleate. Prochlorperazine maleate is designated chemically as 2-chloro-10-[3-(4- methyl-1 -piperazinyl)propyl] phenothiazine maleate [molecular weight 606.10] and has the following structure

Prochlorperazine Maleate is classified as an anti-emetic and antipsychotic agent. Prochlorperazine maleate is white or pale yellow, practically odorless crystalline powder. It is practically insoluble in water and in alcohol; slightly soluble in warm chloroform.
Each tablet, for oral administration contains prochlorperazine maleate equivalent to 5 mg or 10 mg of prochlorperazine. In addition, each tablet contains the following inactive ingredients: D&C yellow no. 10 aluminum lake, FD&C blue no. 2 aluminum lake, FD&C yellow no. 6 aluminum lake, hydroxypropyl methylcellulose, lactose monohydrate, magnesium stearate, microcrystalline cellulose, polyethylene glycol, polysorbate 80, pregelatinized starch, stearic acid and titanium dioxide.

INDICATIONS AND USAGE

For control of severe nausea and vomiting.
For the treatment of schizophrenia.
Prochlorperazine is effective for the short-term treatment of generalized non-psychotic anxiety. However, prochlorperazine is not the first drug to be used in therapy for most patients with non-psychotic anxiety, because certain risks associated with its use are not shared by common alternative treatments (e.g., benzodiazepines).
When used in the treatment of non-psychotic anxiety, prochlorperazine should not be administered at doses of more than 20 mg per day or for longer than 12 weeks, because the use of prochlorperazine at higher doses or for longer intervals may cause persistent tardive dyskinesia that may prove irreversible (see WARNINGS).
The effectiveness of prochlorperazine as treatment for non-psychotic anxiety was established in 4-week clinical studies of outpatients with generalized anxiety disorder. This evidence does not predict that prochlorperazine will be useful in patients with other non-psychotic conditions in which anxiety, or signs that mimic anxiety, are found (e.g., physical illness, organic mental conditions, agitated depression, character pathologies, etc.).
Prochlorperazine has not been shown effective in the management of behavioral complications in patients with mental retardation.

CONTRAINDICATIONS

Do not use in patients with known hypersensitivity to phenothiazines.
Do not use in comatose states or in the presence of large amounts of central nervous system depressants (alcohol, barbiturates, narcotics, etc.).
Do not use in pediatric surgery.
Do not use in pediatric patients under 2 years of age or under 20 lbs. Do not use in children for conditions for which dosage has not been established.

WARNINGS

Increased Mortality in Elderly Patients with Dementia-Related Psychosis
Elderly patients with dementia-related psychosis treated with antipsychotic drugs are at an increased risk of death. Prochlorperazine maleate is not approved for the treatment of patients with dementia-related psychosis (see BOXED WARNING).
The extrapyramidal symptoms which can occur secondary to prochlorperazine may be confused with the central nervous system signs of an undiagnosed primary disease responsible for the vomiting, e.g., Reye’s syndrome or other encephalopathy. The use of prochlorperazine and other potential hepatotoxins should be avoided in children and adolescents whose signs and symptoms suggest Reye’s syndrome.

Tardive Dyskinesia: Tardive dyskinesia, a syndrome consisting of potentially irreversible, involuntary, dyskinetic movements, may develop in patients treated with antipsychotic drugs. Although the prevalence of the syndrome appears to be highest among the elderly, especially elderly women, it is impossible to rely upon prevalence estimates to predict, at the inception of antipsychotic drug treatment, which patients are likely to develop the syndrome. Whether antipsychotic drug products differ in their potential to cause tardive dyskinesia is unknown.
Both the risk of developing the syndrome and the likelihood that it will become irreversible are believed to increase as the duration of treatment and the total cumulative dose of antipsychotic drugs administered to the patient increase. However, the syndrome can develop, although much less commonly, after relatively brief treatment periods at low doses.
There is no known treatment for established cases of tardive dyskinesia, although the syndrome may remit, partially or completely, if antipsychotic drug treatment is withdrawn. Antipsychotic drug treatment itself, however, may suppress (or partially suppress) the signs and symptoms of the syndrome and thereby may possibly mask the underlying disease process.
The effect that symptomatic suppression has upon the long-term course of the syndrome is unknown.
Given these considerations, antipsychotic drugs should be prescribed in a manner that is most likely to minimize the occurrence of tardive dyskinesia especially in the elderly. Chronic antipsychotic treatment should generally be reserved for patients who suffer from a chronic illness that, 1) is known to respond to antipsychotic drugs, and 2) for whom alternative, equally effective, but potentially less harmful treatments are not available or appropriate. In patients who do require chronic treatment, the smallest dose and the shortest duration of treatment producing a satisfactory clinical response should be sought. The need for continued treatment should be reassessed periodically.
If signs and symptoms of tardive dyskinesia appear in a patient on antipsychotics, drug discontinuation should be considered. However, some patients may require treatment despite the presence of the syndrome.
For further information about the description of tardive dyskinesia and its clinical detection, please refer to the sections on PRECAUTIONS and ADVERSE REACTIONS.

Neuroleptic Malignant Syndrome (NMS): A potentially fatal syndrome complex sometimes referred to as neuroleptic Malignant Syndrome (NMS) has been reported in association with antipsychotic drugs. Clinical manifestations of NMS are hyperpyrexia, muscle rigidity, altered mental status and evidence of autonomic instability (irregular pulse or blood pressure, tachycardia, diaphoresis and cardiac dysrhythmias).
The diagnostic evaluation of patients with this syndrome is complicated. In arriving at a diagnosis, it is important to identify cases where the clinical presentation includes both serious medical illness (e.g., pneumonia, systemic infection, etc.) and untreated or inadequately treated extrapyramidal signs and symptoms (EPS). Other important considerations in the differential diagnosis include central anticholinergic toxicity, heat stroke, drug fever and primary central nervous systems (CNS) pathology.
The management of NMS should include 1) immediate discontinuation of antipsychotic drugs and other drugs not essential to concurrent therapy, 2) intensive symptomatic treatment and medical monitoring, and 3) treatment of any concomitant serious medical problems for which specific treatments are available. There is no general agreement about specific pharmacological treatment regimens for uncomplicated NMS.
If a patient requires antipsychotic drug treatment after recovery from NMS, the potential reintroduction of drug therapy should be carefully considered. The patient should be carefully monitored, since recurrences of NMS have been reported.
An encephalopathic syndrome (characterized by weakness, lethargy, fever, tremulousness and confusion, extrapyramidal symptoms, leukocytosis, elevated serum enzymes, BUN and FBS) has occurred in a few patients treated with lithium plus an antipsychotic. In some instances, the syndrome was followed by irreversible brain damage. Because of a possible causal relationship between these events and the concomitant administration of lithium and antipsychotics, patients receiving such combined therapy should be monitored closely for early evidence of neurologic toxicity and treatment discontinued promptly if such signs appear. This encephalopathic syndrome may be similar to or the same as neuroleptic malignant syndrome (NMS).
Patients with bone marrow depression or who have previously demonstrated a hypersensitivity reaction (e.g., blood dyscrasias, jaundice) with a phenothiazine should not receive any phenothiazine, including Prochlorperazine, unless in the judgment of the physician the potential benefits of treatment outweigh the possible hazards.
Prochlorperazine may impair mental and/or physical abilities, especially during the first few days of therapy. Therefore, caution patients about activities requiring alertness (e.g., operating vehicles or machinery).
Phenothiazines may intensify or prolong the action of central nervous system depressants (e.g., alcohol, anesthetics, narcotics).

Falls: Prochlorperazine Maleate Tablets may cause somnolence, postural hypotension, motor and sensory instability, which may lead to falls and, consequently, fractures or other injuries. For patients with diseases, conditions, or medications that could exacerbate these effects, complete fall risk assessments when initiating antipsychotic treatment and recurrently for patients on long-term antipsychotic therapy.

Usage in Pregnancy: Safety for the use of prochlorperazine during pregnancy has not been established. Therefore, prochlorperazine is not recommended for use in pregnant patients except in cases of severe nausea and vomiting that are so serious and intractable that, in the judgment of the physician, drug intervention is required and potential benefits outweigh possible hazards.
There have been reported instances of prolonged jaundice, extrapyramidal signs, hyperreflexia or hyporeflexia in newborn infants whose mothers received phenothiazines.

Non-teratogenic Effects
Neonates exposed to antipsychotic drugs, during third trimester of pregnancy are at risk for extrapyramidal and/or withdrawal symptoms following delivery. There have been reports of agitation, hypertonia, hypotonia, tremor, somnolence, respiratory distress and feeding disorder in these neonates. These complications have varied in severity; while in some cases symptoms have been self-limited, in other cases neonates have required intensive care unit support and prolonged hospitalization.

Prochlorperazine Maleate should be used during pregnancy only if the potential benefit justifies the potential risk to the fetus.

Nursing Mothers: There is evidence that phenothiazines are excreted in the breast milk of nursing mothers. Caution should be exercised when prochlorperazine is administered to a nursing woman.

PRECAUTIONS

Leukopenia, Neutropenia and Agranulocytosis:
In clinical trial and postmarketing experience, events of leukopenia/neutropenia and agranulocytosis have been reported temporally related to antipsychotic agents.
Possible risk factors for leukopenia/neutropenia include preexisting low white blood cell count (WBC) and history of drug induced leukopenia/neutropenia. Patients with a pre-existing low WBC or a history of drug induced leukopenia/neutropenia should have their complete blood count (CBC) monitored frequently during the first few months of therapy and should discontinue Prochlorperazine Maleate Tablets USP at the first sign of a decline in WBC in the absence of other causative factors.
Patients with neutropenia should be carefully monitored for fever or other symptoms or signs of infection and treated promptly if such symptoms or signs occur. Patients with severe neutropenia (absolute neutrophil count < 1000/mm^3) should discontinue Prochlorperazine Maleate Tablets USP and have their WBC followed until recovery.
The antiemetic action of prochlorperazine may mask the signs and symptoms of overdosage of other drugs and may obscure the diagnosis and treatment of other conditions such as intestinal obstruction, brain tumor and Reye’s syndrome (see WARNINGS).
When prochlorperazine is used with cancer chemotherapeutic drugs, vomiting as a sign of the toxicity of these agents may be obscured by the antiemetic effect of prochlorperazine.
Because hypotension may occur, large doses and parenteral administration should be used cautiously in patients with impaired cardiovascular systems. To minimize the occurrence of hypotension after injection, keep patient lying down and observe for at least ^1/2 hour. If hypotension occurs after parenteral or oral dosing, place patient in head-low position with legs raised. If a vasoconstrictor is required, Levophed®* and Neo-Synephrine®** are suitable. Other pressor agents, including epinephrine, should not be used because they may cause a paradoxical further lowering of blood pressure.
Aspiration of vomitus has occurred in a few post-surgical patients who have received prochlorperazine as an antiemetic. Although no causal relationship has been established, this possibility should be borne in mind during surgical aftercare.
Deep sleep, from which patients can be aroused, and coma have been reported, usually with overdosage.
Antipsychotic drugs elevate prolactin levels; the elevation persists during chronic administration. Tissue culture experiments indicate that approximately 1/3 of human breast cancers are prolactin-dependent in vitro, a factor of potential importance if the prescribing of these drugs is contemplated in a patient with a previously detected breast cancer. Although disturbances such as galactorrhea, amenorrhea, gynecomastia and impotence have been reported, the clinical significance of elevated serum prolactin levels is unknown for most patients. An increase in mammary neoplasms has been found in rodents after chronic administration of antipsychotic drugs. Published epidemiologic studies have shown inconsistent results when exploring the association between hyperprolactinemia and breast cancer.
Chromosomal aberrations in spermatocytes and abnormal sperm have been demonstrated in rodents treated with certain antipsychotics.
As with all drugs which exert an anticholinergic effect, and/or cause mydriasis, prochlorperazine should be used with caution in patients with glaucoma.
Because phenothiazines may interfere with thermoregulatory mechanisms, use with caution in persons who will be exposed to extreme heat.
Phenothiazines can diminish the effect of oral anticoagulants.
Phenothiazines can produce alpha-adrenergic blockade.
Thiazide diuretics may accentuate the orthostatic hypotension that may occur with phenothiazines. Antihypertensive effects of guanethidine and related compounds may be counteracted when phenothiazines are used concomitantly.
Concomitant administration of propranolol with phenothiazines results in increased plasma levels of both drugs.
Phenothiazines may lower the convulsive threshold; dosage adjustments of anticonvulsants may be necessary. Potentiation of anticonvulsant effects does not occur. However, it has been reported that phenothiazines may interfere with the metabolism of Dilantin®*** and thus precipitate Dilantin toxicity.
The presence of phenothiazines may produce false-positive phenylketonuria (PKU) test results.

Long-Term Therapy: Given the likelihood that some patients exposed chronically to antipsychotics will develop tardive dyskinesia, it is advised that all patients in whom chronic use is contemplated be given, if possible, full information about this risk. The decision to inform patients and/or their guardians must obviously take into account the clinical circumstances and the competency of the patient to understand the information provided.
To lessen the likelihood of adverse reactions related to cumulative drug effect, patients with a history of long-term therapy with prochlorperazine and/or other antipsychotics should be evaluated periodically to decide whether the maintenance dosage could be lowered or drug therapy discontinued.
Children with acute illnesses (e.g., chickenpox, CNS infections, measles, gastroenteritis) or dehydration seem to be much more susceptible to neuromuscular reactions, particularly dystonias, than are adults. In such patients, the drug should be used only under close supervision.
Drugs which lower the seizure threshold, including phenothiazine derivatives should not be used with Amipaque®§. As with other phenothiazine derivatives, prochlorperazine should be discontinued at least 48 hours before myelography, should not be resumed for at least 24 hours postprocedure, and should not be used for the control of nausea and vomiting occurring either prior to myelography with Amipaque, or post-procedure.

Geriatric Use: Clinical studies of Prochlorperazine did not include sufficient numbers of subjects aged 65 and over to determine whether elderly subjects respond differently from younger subjects. Geriatric patients are more sensitive to the side effects of antipsychotics, including Prochlorperazine. These adverse events include hypotension, anticholinergic effects (such as urinary retention, constipation, and confusion), and neuromuscular reactions (such as parkinsonism and tardive dyskinesia)(see PRECAUTIONS and ADVERSE REACTIONS). Also, postmarketing safety experience suggests that the incidence of agranulocytosis may be higher in geriatric patients compared to younger individuals who received Prochlorperazine. In general, dose selection for an elderly patient should be cautious, usually starting at the low end of the dosing range, reflecting the greater frequency of decreased hepatic, renal, or cardiac function, and of concomitant disease or other drug therapy (seeDOSAGE AND ADMINISTRATION).

ADVERSE REACTIONS

Drowsiness, dizziness, amenorrhea, blurred vision, skin reactions and hypotension may occur. Neuroleptic Malignant Syndrome (NMS) has been reported in association with antipsychotic drugs (see WARNINGS).
Cholestatic jaundice has occurred. If fever with grippe-like symptoms occurs, appropriate liver studies should be conducted. If tests indicate an abnormality, stop treatment. There have been a few observations of fatty changes in the livers of patients who have died while receiving the drug. No causal relationship has been established.
Leukopenia and agranulocytosis have occurred. Warn patients to report the sudden appearance of sore throat or other signs of infection. If white blood cell and differential counts indicate leukocyte depression, stop treatment and start antibiotic and other suitable therapy.

Neuromuscular (Extrapyramidal) Reactions
These symptoms are seen in a significant number of hospitalized mental patients. They maybe characterized by motor restlessness, be of the dystonic type, or they may resemble parkinsonism.
Depending on the severity of symptoms, dosage should be reduced or discontinued. If therapy is reinstituted, it should be at a lower dosage. Should these symptoms occur in children or pregnant patients, the drug should be stopped and not reinstituted. In most cases barbiturates by suitable route of administration will suffice. (Or, injectable Benadryl®ll may be useful). In more severe cases, the administration of an anti-parkinsonism agent, except levodopa (See PDR), usually produces rapid reversal of symptoms. Suitable supportive measures such as maintaining a clear airway and adequate hydration should be employed.

Dystonia
Class effect: Symptoms of dystonia, prolonged abnormal contractions of muscle groups, may occur in susceptible individuals during the first few days of treatment. Dystonic symptoms include: spasm of the neck muscles, sometimes progressing to tightness of the throat, swallowing difficulty, difficulty breathing, and/or protrusion of the tongue. While these symptoms can occur at low doses, they occur more frequently and with greater severity with high potency and at higher doses of first generation antipsychotic drugs. An elevated risk of acute dystonia is observed in males and younger age groups.
These usually subside within a few hours, and almost always within 24 to 48 hours, after the drug has been discontinued.

Motor Restlessness: Symptoms may include agitation or jitteriness and sometimes insomnia. These symptoms often disappear spontaneously. At times these symptoms may be similar to the original neurotic or psychotic symptoms. Dosage should not be increased until these side effects have subsided.
If these symptoms become too troublesome, they can usually be controlled by a reduction of dosage or change of drug. Treatment with anti-parkinsonian agents, benzodiazepines or propranolol may be helpful.

Pseudo-Parkinsonism: Symptoms may include: mask-like facies; drooling; tremors; pillrolling motion; cog-wheel rigidity; and shuffling gait. Reassurance and sedation are important. In most cases these symptoms are readily controlled when an anti-parkinsonism agent is administered concomitantly. Anti- parkinsonism agents should be used only when required. Generally, therapy of a few weeks to 2 or 3 months will suffice. After this time patients should be evaluated to determine their need for continued treatment. (Note: Levodopa has not been found effective in pseudo-parkinsonism). Occasionally it is necessary to lower the dosage of prochlorperazine or to discontinue the drug.

Tardive Dyskinesia: As with all antipsychotic agents, tardive dyskinesia may appear in some patients on long-term therapy or may appear after drug therapy has been discontinued. The syndrome can also develop, although much less frequently, after relatively brief treatment periods at low doses. This syndrome appears in all age groups. Although its prevalence appears to be highest among elderly patients, especially elderly women, it is impossible to rely upon prevalence estimates to predict at the inception of antipsychotic treatment which patients are likely to develop the syndrome. The symptoms are persistent and in some patients appear to be irreversible. The syndrome is characterized by rhythmical involuntary movements of the tongue, face, mouth or jaw (e.g., protrusion of tongue, puffing of cheeks, puckering of mouth, chewing movements). Sometimes these may be accompanied by involuntary movements of extremities. In rare instances, these involuntary movements of the extremities are the only manifestations of tardive dyskinesia. A variant of tardive dyskinesia, tardive dystonia, has also been described.
There is no known effective treatment for tardive dyskinesia; anti-parkinsonism agents do not alleviate the symptoms of this syndrome. It is suggested that all antipsychotic agents be discontinued if these symptoms appear.
Should it be necessary to reinstitute treatment, or increase the dosage of the agent, or switch to a different antipsychotic agent, the syndrome may be masked.
It has been reported that fine vermicular movements of the tongue may be an early sign of the syndrome and if the medication is stopped at that time the syndrome may not develop.

Adverse Reactions Reported with Prochlorperazine or Other Phenothiazine Derivatives:
Adverse reactions with different phenothiazines vary in type, frequency and mechanism of occurrence, i.e., some are dose-related, while others involve individual patient sensitivity. Some adverse reactions may be more likely to occur, or occur with greater intensity, in patients with special medical problems, e.g., patients with mitral insufficiency or pheochromocytoma have experienced severe hypotension following recommended doses of certain phenothiazines.
Not all of the following adverse reactions have been observed with every phenothiazine derivative, but they have been reported with 1 or more and should be borne in mind when drugs of this class are administered: extrapyramidal symptoms (opisthotonos, oculogyric crisis, hyperreflexia, dystonia, akathisia, dyskinesia, parkinsonism) some of which have lasted months and even years-particularly in elderly patients with previous brain damage; grand mal and petit mal convulsions, particularly in patients with EEG abnormalities or history of such disorders; altered cerebrospinal fluid proteins; cerebral edema; intensification and prolongation of the action of central nervous system depressants (opiates, analgesics, antihistamines, barbiturates, alcohol), atropine, heat, organophosphorus insecticides; autonomic reactions (dryness of mouth, nasal congestion, headache, nausea, constipation, obstipation, adynamic ileus, ejaculatory disorders/impotence, priapism, atonic colon, urinary retention, miosis and mydriasis); reactivation of psychotic processes, catatonic-like states; hypotension (sometimes fatal); cardiac arrest; blood dyscrasias (pancytopenia, thrombocytopenic purpura, leukopenia, agranulocytosis, eosinophilia, hemolytic anemia, aplastic anemia); liver damage (jaundice, biliary stasis); endocrine disturbances (hyperglycemia, hypoglycemia, glycosuria, lactation, galactorrhea, gynecomastia, menstrual irregularities, false-positive pregnancy tests); skin disorders (photosensitivity, itching, erythema, urticaria, eczema up to exfoliative dermatitis); other allergic reactions (asthma, laryngeal edema, angioneurotic edema, anaphylactoid reactions); peripheral edema; reversed epinephrine effect; hyperpyrexia; mild fever after large I.M. doses; increased appetite; increased weight; a systemic lupus erythematosus-like syndrome; pigmentary retinopathy; with prolonged administration of substantial doses, skin pigmentation, epithelial keratopathy, and lenticular and corneal deposits.
EKG changes- particularly nonspecific, usually reversible Q and T wave distortions-have been observed in some patients receiving phenothiazine.
Although phenothiazines cause neither psychic nor physical dependence, sudden discontinuance in long-term psychiatric patients may cause temporary symptoms, e.g., nausea and vomiting, dizziness, tremulousness.
NOTE: There have been occasional reports of sudden death in patients receiving phenothiazines. In some cases, the cause appeared to be cardiac arrest or asphyxia due to failure of the cough reflex.

OVERDOSAGE

(See also ADVERSE REACTIONS.)
SYMPTOMS--Primarily involvement of the extrapyramidal mechanism producing some of the dystonic reactions described above.
Symptoms of central nervous system depression to the point of somnolence or coma. Agitation and restlessness may also occur. Other possible manifestations include convulsions, EKG changes and cardiac arrhythmias, fever and autonomic reactions such as hypotension, dry mouth and ileus.
TREATMENT--It is important to determine other medications taken by the patient since multiple-dose therapy is common in overdosage situations. Treatment is essentially symptomatic and supportive. Early gastric lavage is helpful. Keep patient under observation and maintain an open airway, since involvement of the extrapyramidal mechanism may produce dysphagia and respiratory difficulty in severe overdosage. Do not attempt to induce emesis because a dystonic reaction of the head or neck may develop that could result in aspiration of vomitus. Extrapyramidal symptoms may be treated with antiparkinsonism drugs, barbiturates or Benadryl. See prescribing information for these products. Care should be taken to avoid increasing respiratory depression.
If administration of a stimulant is desirable, amphetamine, dextroamphetamine or caffeine with sodium benzoate is recommended.
Stimulants that may cause convulsions (e.g., picrotoxin or pentylenetetrazol) should be avoided.
If hypotension occurs, the standard measures for managing circulatory shock should be initiated. If it is desirable to administer a vasoconstrictor, Levophed and Neo-Synephrine are most suitable. Other pressor agents, including epinephrine, are not recommended because phenothiazine derivatives may reverse the usual elevating action of these agents and cause further lowering of blood pressure.
Limited experience indicates that phenothiazines are not dialyzable.

DOSAGE & ADMINISTRATION - ADULTS

(For children’s dosage and administration, see below.) Dosage should be increased more gradually in debilitated or emaciated patients.

Elderly Patients: In general, dosages in the lower range are sufficient for most elderly patients. Since they appear to be more susceptible to hypotension and neuromuscular reactions, such patients should be observed closely. Dosage should be tailored to the individual, response carefully monitored and dosage adjusted accordingly. Dosage should be increased more gradually in elderly patients.

1.To Control Severe Nausea and Vomiting:
Adjust dosage to the response of the individual. Begin with the lowest recommended dosage.
Oral Dosage-Tablets: Usually one 5mg or 10mg tablet 3 or 4 times daily. Daily dosages above 40 mgs should be used only in resistant cases.

2.In Adult Psychiatric Disorders: Adjust dosage to the response of the individual and according to the severity of the condition. Begin with the lowest recommended dose. Although response ordinarily is seen within a day or 2, longer treatment is usually required before maximal improvement is seen.
Oral Dosage: Non-Psychotic Anxiety--Usual dosage is 5 mg 3 or4 times daily. Do not administer in doses of more than 20mg per day or for longer than 12 weeks.

Psychotic Disorders including Schizophrenia--In relatively mild conditions, as seen in private psychiatric practice or in out patient clinics, dosage is 5 or 10 mg 3 or 4 times daily.

In moderate to severe conditions, for hospitalized or adequately supervised patients, usual starting dosage is 10 mg 3 or 4 times daily. Increase dosage gradually until symptoms are controlled or side effects become bothersome. When dosage is increased by small increments every 2 or 3 days, side effects either do not occur or are easily controlled. Some patients respond satisfactorily on 50 to 75mg daily.

In more severe disturbances, optimum dosage is usually 100 to 150mg daily.

DOSAGE AND ADMINISTRATION--CHILDREN

Do not use in pediatric surgery.
Children seem more prone to develop extrapyramidal reactions, even on moderate doses. Therefore, use lowest effective dosage. Tell parents not to exceed prescribed dosage, since the possibility for adverse reactions increases as dosage rises.
Occasionally the patient may react to the drug with signs of restlessness and excitement; if this occurs, do not administer additional doses. Take particular precaution in administering the drug to children with acute illnesses or dehydration (see under Dystonias).

1. Severe Nausea and Vomiting in Children:
Prochlorperazine should not be used in pediatric patients under 20 pounds in weight or 2 years of age. It should not be used in conditions for which children’s dosages have not been established. Dosage and frequency of administration should be adjusted according to the severity of the symptoms and the response of the patient. The duration of activity following intramuscular administration may last up to 12 hours. Subsequent doses may be given by the same route if necessary.

Oral Dosage: More than 1 day’s therapy is seldom necessary.

Weight | Usual Dosage | Not to Exceed
under 20 lbs not recommended
20 to 29 lbs | 2½ mg 1 or 2 times a day | 7.5 mg per day
30 to 39 lbs | 2½ mg 2 or 3 times a day | 10 mg per day
40 to 85 lbs | 2½ mg 3 times a day or 5 mg 2 times a day | 15 mg per day

2. Children with schizophrenia:
Oral Dosage: For children 2 to 12 years, starting dosage is 2^1/2 mg 2 or 3 times daily. Do not give more than 10 mg the first day. Then increase dosage according to patient’s response.
FOR AGES 2 to 5, total daily dosage usually does not exceed 20 mg.
FOR AGES 6 to 12, total daily dosage usually does not exceed 25 mg.

HOW SUPPLIED

Product: 50090-2241

Product: 50090-2839

NDC: 50090-2839-0 30 TABLET in a BOTTLE

STORAGE

Store at 20 to 25°C (68 to 77°F) [See USP Controlled Room Temperature].
Protect from light. Dispense in a tight, light-resistant container.

* norepinephrine bitartrate, Abbott Laboratories.
** phenylephrine hydrochloride, Abbott Laboratories.
*** phenytoin, Parke Davis.
§ metrizamide, Sanofi Pharmaceuticals.
ll diphenhydramine hydrochloride, Parke Davis.

Marketed by:
Jubilant Cadista Pharmaceuticals Inc.
Yardley, PA 19607, USA

Revised: 07/2025